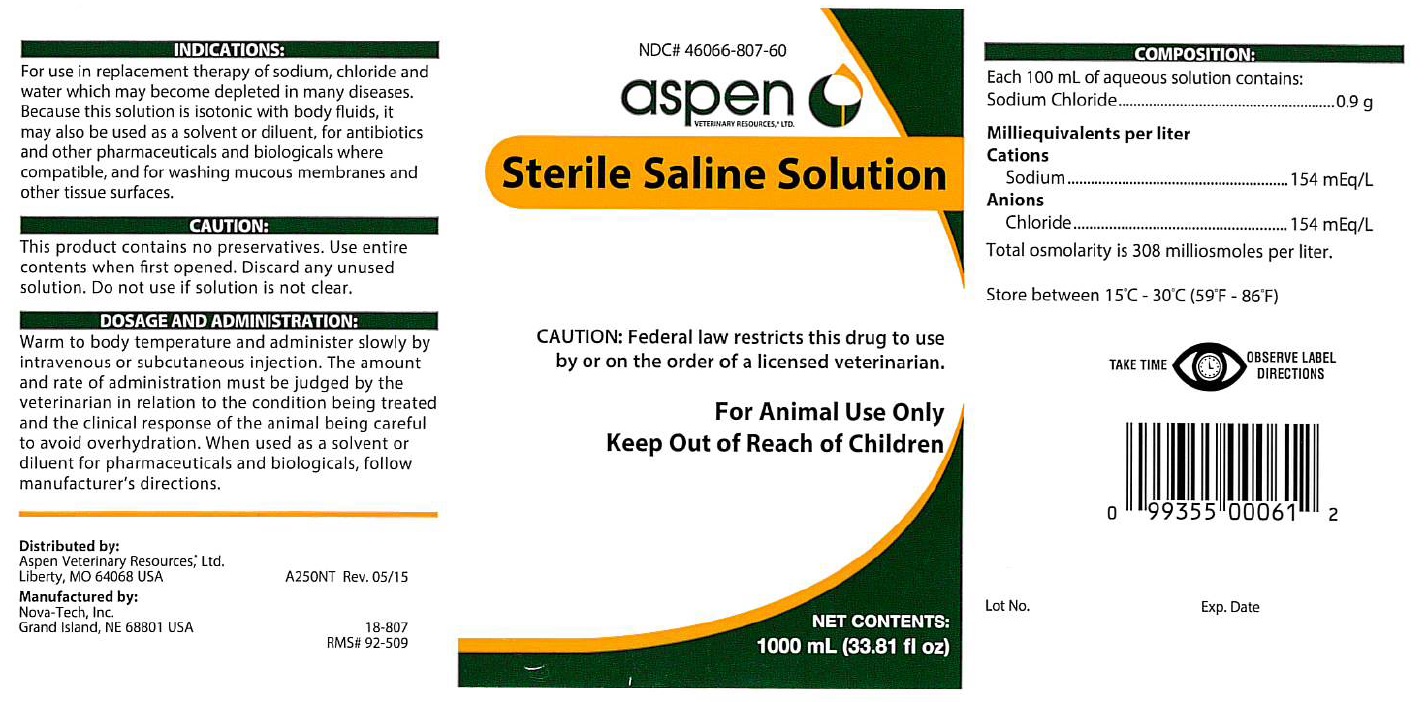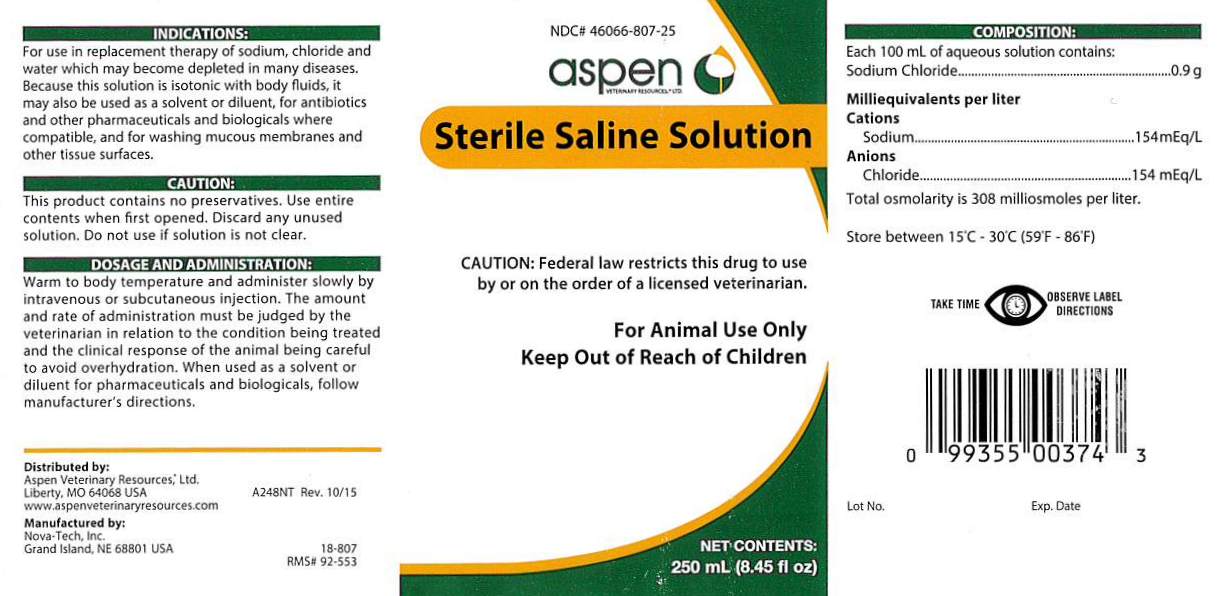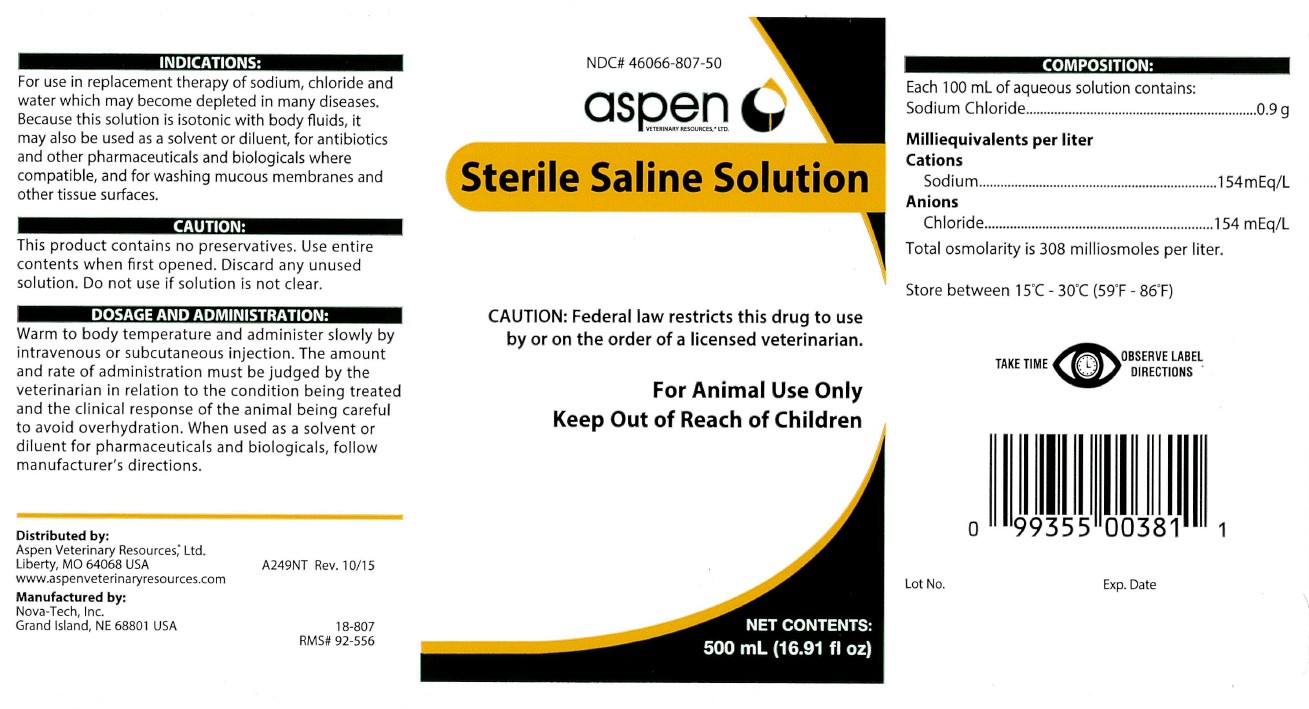 DRUG LABEL: Sterile Saline
NDC: 46066-807 | Form: INJECTION, SOLUTION
Manufacturer: Aspen Veterinary
Category: animal | Type: PRESCRIPTION ANIMAL DRUG LABEL
Date: 20250716

ACTIVE INGREDIENTS: Sodium Chloride 0.9 g/100 mL

Sterile Saline Solution

INDICATIONS:

For use in replacement therapy of sodium, chloride and
water which may become depleted in many diseases.
Because this solution is isotonic with body fluids, it
may also be used as a solvent or diluent, for antibiotics
and other pharmaceuticals and biologicals where
compatible, and for washing mucous membranes and
other tissue surfaces.

CAUTION:

This product contains no preservatives. Use entire
contents when first opened. Discard any unused
solution. Do not use if solution is not clear.

DOSAGE AND ADMINISTRATION:

Warm to body temperature and administer slowly by
intravenous or subcutaneous injection. The amount
and rate of administration must be judged by the
veterinarian in relation to the condition being treated
and the clinical response of the animal being careful
to avoid overhydration. When used as a solvent or
diluent for pharmaceuticals and biologicals, follow
manufacturer's directions.

COMPOSITION:

Each 100 mL of aqueous solution contains:
Sodium Chloride.................................0.9 g
Milliequivalents per liter
Cations
Sodium..............................154 mEq/L
Anions
Chloride.............................154 mEq/L
Total osmolarity is 308 milliosmoles per liter.

STORAGE AND HANDLING

Store between 15°C - 30°C (59°F - 86°F)

CAUTION:

Federal law restricts this drug to use
by or on the order of a licensed veterinarian.

VETERINARY INDICATIONS

For Animal Use Only

Keep Out of Reach of Children

TAKE TIME OBSERVE LABEL DIRECTIONS

INFORMATION FOR OWNERS/CAREGIVERS

Distributed by:
Aspen Veterinary Resources®, Ltd.
Liberty, MO 64068 USA

www.aspenveterinaryresources.com

A250NT Rev. 05/15

Maufactured by:
Nova-Tech, Inc.
Grand Island, NE 68801 USA

18-807
RMS# 92-509

NDC# 46066-807-60

NET CONTENTS:
1000 mL (33.81 fl oz)

Lot No.

Exp. Date